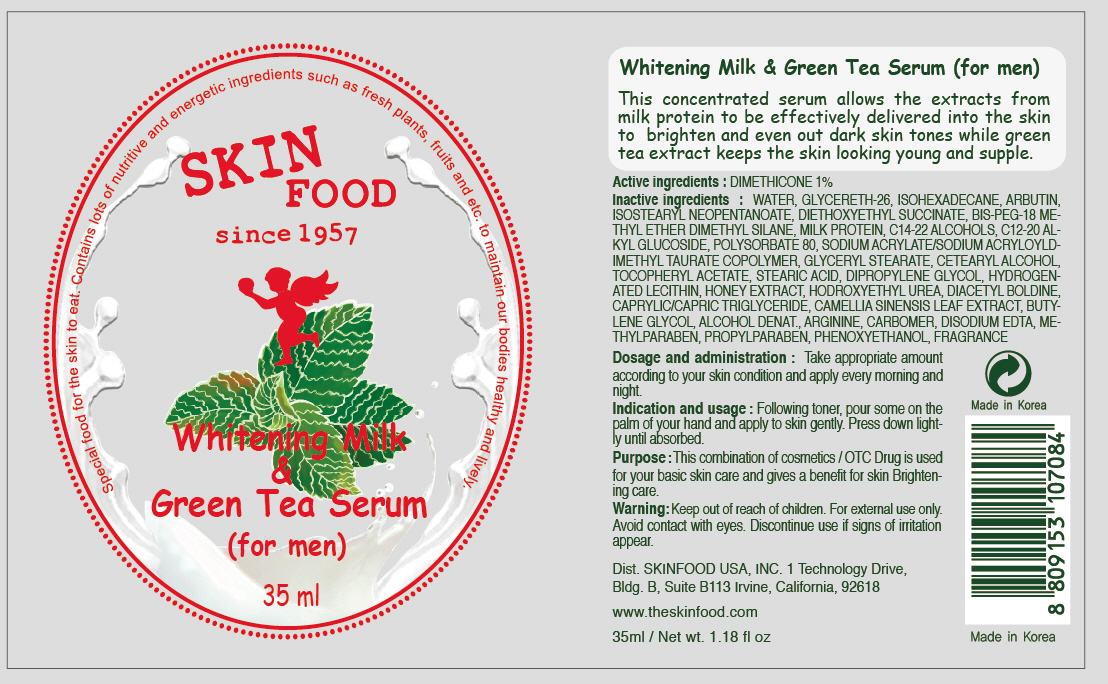 DRUG LABEL: WHITENING MILK AND GREEN TEA SERUM
NDC: 76214-020 | Form: CREAM
Manufacturer: SKINFOOD CO., LTD.
Category: otc | Type: HUMAN OTC DRUG LABEL
Date: 20110920

ACTIVE INGREDIENTS: DIMETHICONE 0.35 mL/35 mL
INACTIVE INGREDIENTS: WATER; GLYCERETH-26; ISOHEXADECANE; ARBUTIN; C14-22 ALCOHOLS; C12-20 ALKYL GLUCOSIDE; POLYSORBATE 80; GLYCERYL MONOSTEARATE; CETOSTEARYL ALCOHOL; METHYLPARABEN; STEARIC ACID; DIPROPYLENE GLYCOL; HYDROGENATED SOYBEAN LECITHIN; HONEY; MEDIUM-CHAIN TRIGLYCERIDES; GREEN TEA LEAF; BUTYLENE GLYCOL; PROPYLPARABEN; PHENOXYETHANOL; ARGININE; EDETATE DISODIUM

Drug Facts

Active ingredient: DIMETHICONE 1%

Inactive ingredients:
WATER, GLYCERETH-26, ISOHEXADECANE, ARBUTIN, ISOSTEARYL NEOPENTANOATE, DIETHOXYETHYL SUCCINATE, BIS-PEG-18 METHYL ETHER DIMETHYL SILANE, MILK PROTEIN, C14-22 ALCOHOLS, C12-20 ALKYL GLUCOSIDE, POLYSORBATE 80, SODIUM ACRYLATE/SODIUM ACRYLOYLDIMETHYL TAURATE COPOLYMER, GLYCERYL STEARATE, CETEARYL ALCOHOL, TOCOPHERYL ACETATE, STEARIC ACID, DIPROPYLENE GLYCOL, HYDROGENATED LECITHIN, HONEY EXTRACT, HODROXYETHYL UREA, DIACETYL BOLDINE, CAPRYLIC/CAPRIC, TRIGLYCERIDE, CAMELLIA SINENSIS LEAF EXTRACT, BUTYLENE GLYCOL, ALCOHOL DENAT., ARGININE, CARBOMER, DISODIUM EDTA, METHYLPARABEN, PROPYLPARABEN, PHENOXYETHANOL, FRAGRANCE

PURPOSE

Purpose: This combination of cosmetics / OTC Drug is used for your basic skin care and gives a benefit for skin Brightening care.

Warnings:
For external use only.
Avoid contact with eyes.
Discontinue use if signs of irritation appear.

Keep out of reach of children:
Keep out of reach of children.

Indication and usage:
Following toner, pour some on the palm of your hand and apply to skin gently. Press down lightly until absorbed.

Dosage and administration:
Take appropriate amount according to your skin condition and apply every morning and night.